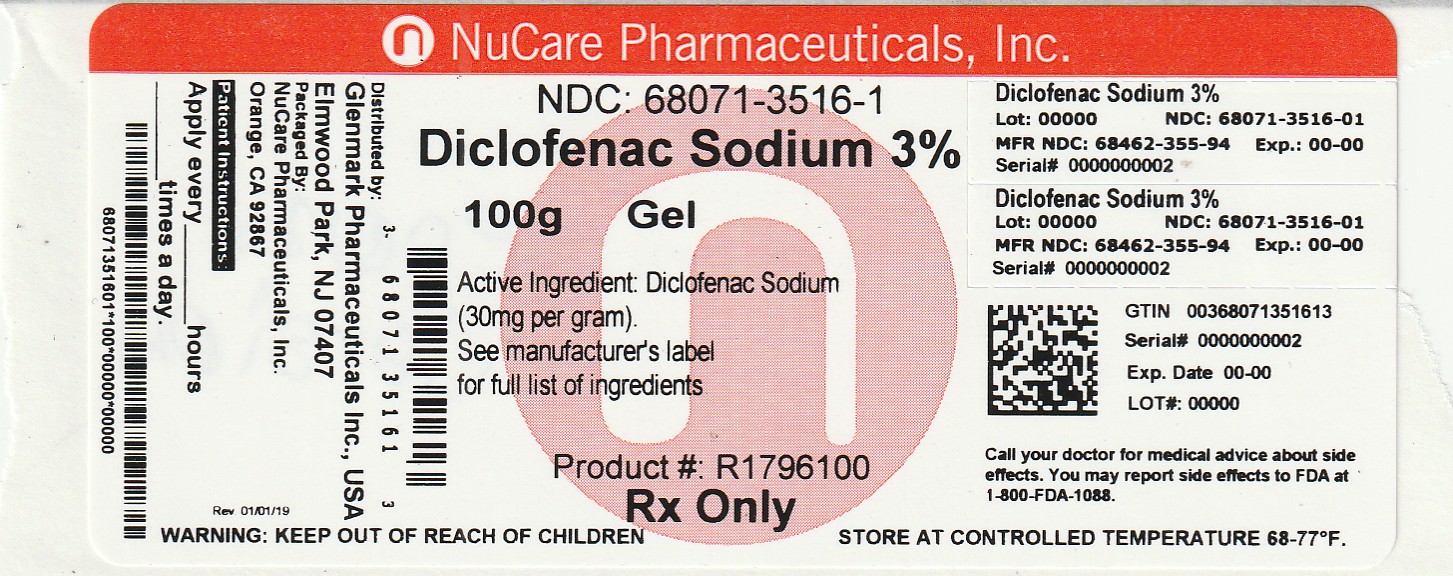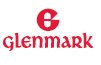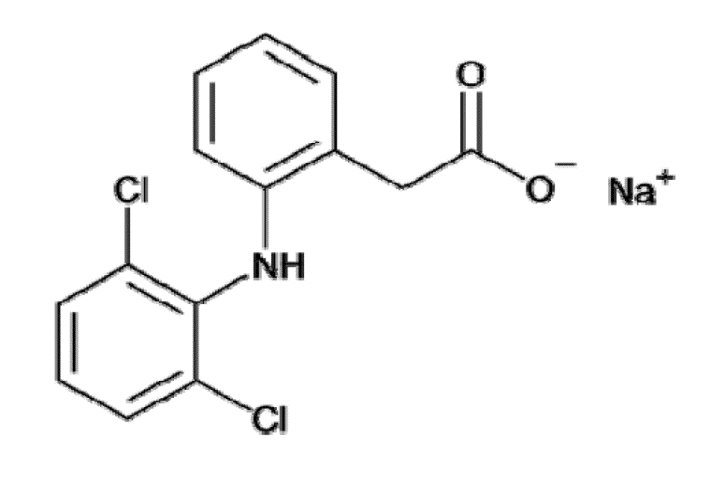 DRUG LABEL: DICLOFENAC SODIUM
NDC: 68071-3516 | Form: GEL
Manufacturer: NuCare Pharmaceuticals,Inc.
Category: prescription | Type: HUMAN PRESCRIPTION DRUG LABEL
Date: 20260216

ACTIVE INGREDIENTS: DICLOFENAC SODIUM 30 mg/1 g
INACTIVE INGREDIENTS: BENZYL ALCOHOL; HYALURONATE SODIUM; PEG-6 METHYL ETHER; WATER

HIGHLIGHTS OF PRESCRIBING INFORMATION

These highlights do not include all the information needed to use DICLOFENAC SODIUM GEL safely and effectively. See full prescribing information for DICLOFENAC SODIUM GEL.
DICLOFENAC SODIUM topical gel
Initial U.S. Approval: 2000

WARNING: RISK OF SERIOUS CARDIOVASCULAR AND GASTROINTESTINAL EVENTS

WARNING: RISK OF SERIOUS CARDIOVASCULAR EVENTS AND GASTROINTESTINAL EVENTS

See full prescribing information for complete boxed warning.

- Nonsteroidal anti-inflammatory drugs (NSAIDs) cause an increased risk of serious cardiovascular thrombotic events, including myocardial infarction and stroke, which can be fatal. This risk may occur early in treatment and may increase with duration of use. (5.4)
- Diclofenac sodium gel is contraindicated in the setting of coronary artery bypass graft (CABG) surgery. (4, 5.4)
- NSAIDs cause an increased risk of serious gastrointestinal (GI) adverse events including bleeding, ulceration, and perforation of the stomach or intestines, which can be fatal. These events can occur at any time during use and without warning symptoms. Elderly patients and patients with a prior history of peptic ulcer disease and/or GI bleeding are at greater risk for serious GI events (5.5)

1 INDICATIONS AND USAGE

Diclofenac sodium gel is a nonsteroidal anti-inflammatory drug (NSAID) indicated for the topical treatment of actinic keratoses (AK). (1)

2 DOSAGE AND ADMINISTRATION

- Use the lowest effective dosage for shortest duration consistent with the individual patient treatment goals. (2)
- Apply to lesion areas twice daily to adequately cover each lesion. (2)
- Use 0.5 g of gel (pea size) on each 5 cm x 5 cm lesion site. (2)
- The recommended duration of therapy is from 60 days to 90 days. Complete healing of the lesion(s) or optimal therapeutic effect may not be evident for up to 30 days following cessation of therapy. Lesions that do not respond to therapy should be re-evaluated and management reconsidered. (2)
- Avoid contact in eyes, nose, or mouth. (2)

3 DOSAGE FORMS AND STRENGTHS

Topical gel, 3%

4 CONTRAINDICATIONS

- Known hypersensitivity to diclofenac or any components of the drug product. (4, 11)
- History of asthma, urticaria, or allergic-type reactions after taking aspirin or other NSAIDs. (4)
- Use on damaged skin. (4)
- In the setting of coronary artery bypass graft (CABG) surgery. (4)

5 WARNINGS AND PRECAUTIONS

- Anaphylactic Reactions: Seek emergency help if an anaphylactic reaction occurs. (5.1)
- Exacerbation of Asthma Related to Aspirin Sensitivity: Diclofenac sodium gel is contraindicated in patients with aspirin-sensitive asthma. Monitor patients with pre-existing asthma (without aspirin sensitivity). (5.2)
- Serious Skin Reactions: Discontinue diclofenac sodium gel at first appearance of skin rash or other signs of hypersensitivity. (5.3, 5.15)
- Hepatoxicity: Inform patients of warning signs and symptoms of hepatotoxicity. Discontinue if abnormal liver tests persist or worsen or if clinical signs and symptoms of liver disease develop. (5.6)
- Hypertension: Patients taking some antihypertensive medications may have impaired response to these therapies when taking NSAIDs. Monitor blood pressure. (5.7, 7)
- Heart Failure and Edema: Avoid use of diclofenac sodium gel in patients with severe heart failure. (5.8)
- Renal Toxicity: Monitor renal function in patients with renal or hepatic impairment, heart failure, dehydration, or hypovolemia. Avoid use of diclofenac sodium gel in patients with advanced renal disease. (5.9)
- Drug Reaction with Eosinophilia and Systemic Symptoms (DRESS): Discontinue diclofenac sodium gel and evaluate clinically. (5.10)
- Fetal Toxicity: Limit use of NSAIDs, including diclofenac sodium gel, between about 20 to 30 weeks in pregnancy due to the risk of oligohydramnios/fetal renal dysfunction. Avoid use of NSAIDs in women at about 30 weeks gestation and later in pregnancy due to the risks of oligohydramnios/fetal renal dysfunction and premature closure of the fetal ductus arteriosus. (5.11, 8.1)
- Hematologic Toxicity: Monitor hemoglobin or hematocrit in patients with any signs or symptoms of anemia. (5.12, 7).
- Photosensitivity: Avoid exposure of treated area(s) to natural or artificial sunlight. (5.15)
- Exposure to Eyes and Mucosal Membranes: Avoid contact of diclofenac sodium gel with eyes and mucosal membranes. (5.16)
- Oral Nonsteroidal Anti-inflammatory Drugs: Avoid concurrent use with oral NSAIDs. (5.17)

6 ADVERSE REACTIONS

Most common adverse reactions with diclofenac sodium gel are application site reactions, including dermatitis. (6)

To report SUSPECTED ADVERSE REACTIONS, contact Glenmark Pharmaceuticals Inc., USA at 1 (888) 721-7115 or FDA at 1-800-FDA-1088 or www.fda.gov/medwatch.

7 DRUG INTERACTIONS

- Drugs that Interfere with Hemostasis (e.g., warfarin, aspirin, SSRIs/SNRIs): Monitor patients for bleeding who are using diclofenac sodium gel concomitantly with drugs that interfere with hemostasis. (7)
- ACE Inhibitors, Angiotensin Receptor Blockers (ARB), or Beta- Blockers: Concomitant use with diclofenac sodium gel may diminish the antihypertensive effect of these drugs. (7)
- ACE Inhibitors and ARBs: Concomitant use with diclofenac sodium gel in elderly, volume depleted, or those with renal impairment may result in deterioration of renal function. (7)
- Diuretics: NSAIDs can reduce natriuretic effect of furosemide and thiazide diuretics. (7)
- Digoxin: Concomitant use with diclofenac sodium gel may increase serum concentration and prolong half-life of digoxin. (7)

8 USE IN SPECIFIC POPULATIONS

Infertility: NSAIDs are associated with reversible infertility. Consider withdrawal of diclofenac sodium gel in women who have difficulties conceiving (8.3)

FULL PRESCRIBING INFORMATION

WARNING: RISK OF SERIOUS CARDIOVASCULAR AND GASTROINTESTINAL EVENTS

Cardiovascular Thrombotic Events

- Nonsteroidal anti-inflammatory drugs (NSAIDs) cause an increased risk of serious cardiovascular thrombotic events, including myocardial infarction and stroke, which can be fatal. This risk may occur early in treatment and may increase with duration of use [see Warnings and Precautions (5.4)] .
- Diclofenac sodium gel is contraindicated in the setting of coronary artery bypass graft (CABG) surgery [see Contraindications (4) and Warnings and Precautions (5.4)] .

Gastrointestinal Bleeding, Ulceration, and Perforation

- NSAIDs cause an increased risk of serious gastrointestinal (GI) adverse events including bleeding, ulceration, and perforation of the stomach or intestines, which can be fatal. These events can occur at any time during use and without warning symptoms. Elderly patients and patients with a prior history of peptic ulcer disease and/or GI bleeding are at a greater risk for serious GI events [see Warnings and Precautions (5.5)] .

1 INDICATIONS AND USAGE

Diclofenac sodium gel is indicated for the topical treatment of actinic keratoses (AK).

2 DOSAGE AND ADMINISTRATION

Use the lowest effective dosage for the shortest duration consistent with individual patient treatment goals [see Warnings and Precautions (5)] .

Apply diclofenac sodium gel gently to lesion areas twice daily. to adequately cover each lesion. Use 0.5 g of gel (pea size) on each 5 cm x 5 cm lesion site. The recommended duration of therapy is from 60 days to 90 days. Complete healing of the lesion(s) or optimal therapeutic effect may not be evident for up to 30 days following cessation of therapy. Lesions that do not respond to therapy should be re-evaluated and management reconsidered. Avoid contact of diclofenac sodium gel with eyes and mucous membranes.

3 DOSAGE FORMS AND STRENGTHS

Topical gel, 3%. Each gram of Diclofenac Sodium Topical Gel contains 30 mg of diclofenac sodium, USP in a clear, transparent, colorless to slightly yellow gel base. Diclofenac Sodium Gel, 3% is supplied in 100 g tubes.

4 CONTRAINDICATIONS

Diclofenac sodium gel is contraindicated in the following patients:

- With known hypersensitivity (e.g., anaphylactic reactions and serious skin reactions) to diclofenac or any components of the drug product [see Warnings and Precautions (5.1, 5.3, 5.10) and Description (11)]
- With the history of asthma, urticaria, or other allergic type reactions after taking aspirin or other NSAIDs. Severe, sometimes fatal, anaphylactic reactions to NSAIDs have been reported in such patients [see Warnings and Precautions (5.1, 5.2)]
- Application on damaged skin resulting from any etiology, including exudative dermatitis, eczema, infected lesions, burns or wounds [see Warnings and Precautions (5.3)]
- In the setting of coronary bypass graft (CABG) surgery [see Warnings and Precautions (5.4)]

5 WARNINGS AND PRECAUTIONS

5.1 Anaphylactic Reactions

Diclofenac has been associated with anaphylactic reactions in patients with and without known hypersensitivity to diclofenac and in patients with aspirin-sensitive asthma [see Contraindications (4) and Warnings and Precautions (5.2)] .

Seek emergency help if an anaphylactic reaction occurs.

5.2 Exacerbation of Asthma Related to Aspirin Sensitivity

A subpopulation of patients with asthma may have aspirin-sensitive asthma which may include chronic rhinosinusitis complicated by nasal polyps; severe, potentially fatal bronchospasm; and/or intolerance to aspirin and other NSAIDs. Because cross-reactivity between aspirin and other NSAIDs has been reported in such aspirin-sensitive patients, diclofenac sodium gel is contraindicated in patients with this form of aspirin sensitivity. When diclofenac sodium gel is used in patients with preexisting asthma (without known aspirin sensitivity), monitor patients for changes in the signs and symptoms of asthma.

5.3 Serious Skin Reactions

NSAIDs, including diclofenac, can cause serious skin adverse reactions such as exfoliative dermatitis, Stevens-Johnson Syndrome (SJS), and toxic epidermal necrolysis (TEN), which can be fatal. These serious events may occur without warning. Inform patients about the signs and symptoms of serious skin reactions, and to discontinue the use of diclofenac sodium gel at the first appearance of skin rash or any other sign of hypersensitivity. Diclofenac sodium gel is contraindicated in patients with previous serious skin reactions to NSAIDs. Do not apply diclofenac sodium gel to open skin wounds, infections, or exfoliative dermatitis, as it may affect absorption and tolerability of the drug [see Contraindications (4)] .

5.4 Cardiovascular Thrombotic Events

Clinical trials of several COX-2 selective and nonselective NSAIDs of up to three years duration have shown an increased risk of serious cardiovascular (CV) thrombotic events, including myocardial infarction (MI) and stroke, which can be fatal. Based on available data, it is unclear that the risk for CV thrombotic events is similar for all NSAIDs. The relative increase in serious CV thrombotic events over baseline conferred by NSAID use appears to be similar in those with and without known CV disease or risk factors for CV disease. However, patients with known CV disease or risk factors had a higher absolute incidence of excess serious CV thrombotic events, due to their increased baseline rate. Some observational studies found that this increased risk of serious CV thrombotic events began as early as the first weeks of treatment. The increase in CV thrombotic risk has been observed most consistently at higher doses.

To minimize the potential risk for an adverse CV event in NSAID-treated patients, use the lowest effective dose for the shortest duration possible. Physicians and patients should remain alert for the development of such events, throughout the entire treatment course, even in the absence of previous CV symptoms. Patients should be informed about the symptoms of serious CV events and the steps to take if they occur.

There is no consistent evidence that concurrent use of aspirin mitigates the increased risk of serious CV thrombotic events associated with NSAID use. The concurrent use of aspirin and an NSAID, such as diclofenac, increases the risk of serious gastrointestinal (GI) events.

Status Post Coronary Artery Bypass Graft (CABG) Surgery

Two controlled clinical trials of a COX-2 selective NSAID for the treatment of pain in the first 10–14 days following CABG surgery found an increased incidence of myocardial infarction and stroke. NSAIDs are contraindicated in the setting of CABG.

Post-MI Patients

Observational studies conducted in the Danish National Registry have demonstrated that patients treated with NSAIDs in the post-MI period were at increased risk of reinfarction, CV-related death, and all-cause mortality beginning in the first week of treatment. In this same cohort, the incidence of death in the first-year post MI was 20 per 100 person years in NSAID-treated patients compared to 12 per 100 person years in non-NSAID exposed patients. Although the absolute rate of death declined somewhat after the first year post-MI, the increased relative risk of death in NSAID users persisted over at least the next four years of follow-up.

Avoid the use of diclofenac sodium gel in patients with a recent MI unless the benefits are expected to outweigh the risk of recurrent CV thrombotic events. If diclofenac sodium gel is used in patients with a recent MI, monitor patients for signs of cardiac ischemia.

5.5 Gastrointestinal Bleeding, Ulceration, and Perforation

NSAIDs, including diclofenac, cause serious GI adverse events including inflammation, bleeding, ulceration, and perforation of the esophagus, stomach, small intestine, or large intestine, which can be fatal. These serious adverse events can occur at any time, with or without warning symptoms, in patients treated with NSAIDs.

Only one in five patients who develop a serious upper GI adverse event on NSAID therapy is symptomatic. Upper GI ulcers, gross bleeding, or perforation caused by NSAIDs occurred in approximately 1% of patients treated for 3 to 6 months, and in about 2% to 4% of patients treated for one year. However, even short-term NSAID therapy is not without risk.

Risk Factors for GI Bleeding, Ulceration, and Perforation

Patients with a prior history of peptic ulcer disease and/or GI bleeding who used NSAIDs had a greater than 10-fold increased risk for developing a GI bleed compared to patients without these risk factors. Other factors that increase the risk of GI bleeding in patients treated with NSAIDs include longer duration of NSAID therapy; concomitant use of oral corticosteroids, aspirin, anticoagulants, or selective serotonin reuptake inhibitors (SSRIs); smoking; use of alcohol; older age; and poor general health status. Most postmarketing reports of fatal GI events occurred in elderly or debilitated patients. Additionally, patients with advanced liver disease and/or coagulopathy are at increased risk for GI bleeding.

Strategies to Minimize the GI Risks in NSAID-Treated Patients:

- Use the lowest effective dosage for the shortest possible duration.
- Avoid administration of more than one NSAID at a time.
- Avoid use in patients at higher risk unless benefits are expected to outweigh the increased risk of bleeding. For such patients, as well as those with active GI bleeding, consider alternate therapies other than NSAIDs.
- Remain alert for signs and symptoms of GI ulceration and bleeding during NSAID therapy.
- If a serious GI adverse event is suspected, promptly initiate evaluation and treatment, and discontinue diclofenac sodium gel until a serious GI adverse event is ruled out.
- In the setting of concomitant use of low-dose aspirin for cardiac prophylaxis, monitor patients more closely for evidence of GI bleeding [see Drug Interactions (7)] .

5.6 Hepatotoxicity

In clinical trials with diclofenac sodium gel, 2 to 3% of subjects had elevations of liver function tests (LFTs) [see Clinical Trials Experience (6.1)]. To minimize the potential risk for an adverse liver-related event in patients treated with diclofenac sodium gel, use the lowest effective dose for the shortest duration possible. Exercise caution when prescribing diclofenac sodium gel with concomitant drugs that are known to be potentially hepatotoxic (e.g., acetaminophen, antibiotics, anti-epileptics).

Physicians should measure transaminases at baseline and periodically in patients receiving long-term therapy with diclofenac, because severe hepatotoxicity may develop without a prodrome of distinguishing symptoms. The optimum times for making the first and subsequent transaminase measurements are not known. Based on clinical trial data and postmarketing experiences, transaminases should be monitored within 4 to 8 weeks after initiating treatment with diclofenac. However, severe hepatic reactions can occur at any time during treatment with diclofenac.

If abnormal liver tests persist or worsen, if clinical signs and/or symptoms consistent with liver disease develop, or if systemic manifestations occur (e.g., eosinophilia, rash, abdominal pain, diarrhea, dark urine, etc.), diclofenac sodium gel should be discontinued immediately.

Inform patients of the warning signs and symptoms of hepatotoxicity (e.g., nausea, fatigue, lethargy, diarrhea, pruritus, jaundice, right upper quadrant tenderness, and “flu-like” symptoms). If clinical signs and symptoms consistent with liver disease develop, or if systemic manifestations occur (e.g., eosinophilia, rash, etc.), discontinue diclofenac sodium gel immediately, and perform a clinical evaluation of the patient.

5.7 Hypertension

NSAIDs, including diclofenac sodium gel, can lead to new onset of hypertension or worsening of pre-existing hypertension, either of which may contribute to the increased incidence of CV events. Patients taking angiotensin converting enzyme (ACE) inhibitors, thiazide diuretics, or loop diuretics may have impaired response to these therapies when taking NSAIDs [see Drug Interactions (7)] .

Monitor blood pressure (BP) during the initiation of NSAID treatment and throughout the course of therapy.

5.8 Heart Failure and Edema

The Coxib and traditional NSAID Trialists’ Collaboration meta-analysis of randomized controlled trials demonstrated an approximately two-fold increase in hospitalizations for heart failure in COX-2 selective-treated patients and nonselective NSAID-treated patients compared to placebo-treated patients. In a Danish National Registry study of patients with heart failure, NSAID use increased the risk of MI, hospitalization for heart failure, and death.

Additionally, fluid retention and edema have been observed in some patients treated with NSAIDs. Use of diclofenac may blunt the CV effects of several therapeutic agents used to treat these medical conditions [e.g., diuretics, ACE inhibitors, or angiotensin receptor blockers (ARBs)].

Avoid the use of diclofenac sodium gel in patients with severe heart failure unless the benefits are expected to outweigh the risk of worsening heart failure. If diclofenac sodium gel is used in patients with severe heart failure, monitor patients for signs of worsening heart failure.

5.9 Renal Toxicity and Hyperkalemia

Renal Toxicity

Long-term administration of NSAIDs has resulted in renal papillary necrosis and other renal injury.

Patients at greatest risk of this reaction are those with impaired renal function, dehydration, hypovolemia, heart failure, liver dysfunction, those taking diuretics and ACE inhibitors or ARBs, and the elderly. Discontinuation of NSAID therapy is usually followed by recovery to the pretreatment state.

No information is available from controlled clinical trials regarding the use of diclofenac sodium gel in patients with advanced renal disease. The renal effects of diclofenac sodium gel may hasten the progression of renal dysfunction in patients with pre-existing renal disease.

Correct volume status in dehydrated or hypovolemic patients prior to initiating diclofenac sodium gel. Monitor renal function in patients with renal or hepatic impairment, heart failure, dehydration, or hypovolemia during use of diclofenac sodium gel [see Drug Interactions (7)] .Avoid the use of diclofenac sodium gel in patients with advanced renal disease unless the benefits are expected to outweigh the risk of worsening renal function. If diclofenac sodium gel is used in patients with advanced renal disease, monitor patients for signs of worsening renal function.

Hyperkalemia

Increases in serum potassium concentration, including hyperkalemia, have been reported with use of NSAIDs, even in some patients without renal impairment. In patients with normal renal function, these effects have been attributed to a hyporeninemic-hypoaldosteronism state.

5.10 Drug Reaction with Eosinophilia and Systemic Symptoms (DRESS)

Drug Reaction with Eosinophilia and Systemic Symptoms (DRESS) has been reported in patients taking NSAIDs such as diclofenac sodium gel. Some of these events have been fatal or life-threatening. DRESS typically, although not exclusively, presents with fever, rash, lymphadenopathy, and/or facial swelling. Other clinical manifestations may include hepatitis, nephritis, hematological abnormalities, myocarditis, or myositis. Sometimes symptoms of DRESS may resemble an acute viral infection. Eosinophilia is often present. Because this disorder is variable in its presentation, other organ systems not noted here may be involved. It is important to note that early manifestations of hypersensitivity, such as fever or lymphadenopathy, may be present even though rash is not evident. If such signs or symptoms are present, discontinue diclofenac sodium gel and evaluate the patient immediately.

5.11 Fetal Toxicity

Premature Closure of Fetal Ductus Arteriosus

Avoid use of NSAIDs, including diclofenac sodium gel, in pregnant women at about 30 weeks gestation and later. NSAIDs, including diclofenac sodium gel, increase the risk of premature closure of the fetal ductus arteriosus at approximately this gestational age.

Oligohydramnios/Neonatal Renal Impairment

Use of NSAIDs, including diclofenac, at about 20 weeks gestation or later in pregnancy may cause fetal renal dysfunction leading to oligohydramnios and, in some cases, neonatal renal impairment. These adverse outcomes are seen, on average, after days to weeks of treatment, although oligohydramnios has been infrequently reported as soon as 48 hours after NSAID initiation. Oligohydramnios is often, but not always, reversible with treatment discontinuation. Complications of prolonged oligohydramnios may, for example, include limb contractures and delayed lung maturation. In some postmarketing cases of impaired neonatal renal function, invasive procedures such as exchange transfusion or dialysis were required.

If, after careful consideration of alternative treatment options for actinic keratoses, NSAID treatment is necessary between about 20 weeks and 30 weeks gestation, limit diclofenac sodium gel use to the lowest effective dose and shortest duration possible. Consider ultrasound monitoring of amniotic fluid if diclofenac treatment extends beyond 48 hours. Discontinue diclofenac sodium gel if oligohydramnios occurs and follow up according to clinical practice [see Use in Specific Populations (8.1)] .

5.12 Hematologic Toxicity

Anemia has occurred in NSAID-treated patients. This may be due to occult or gross blood loss, fluid retention, or an incompletely described effect on erythropoiesis. If a patient treated with diclofenac sodium gel has any signs or symptoms of anemia, monitor hemoglobin or hematocrit.

NSAIDs, including diclofenac sodium gel, may increase the risk of bleeding events. Co-morbid conditions such as coagulation disorders, concomitant use of warfarin, other anticoagulants, antiplatelet agents (e.g., aspirin), serotonin reuptake inhibitors (SSRIs) and serotonin norepinephrine reuptake inhibitors (SNRIs) may increase this risk. Monitor these patients for signs of bleeding [see Drug Interactions (7)] .

5.13 Masking of Inflammation and Fever

The pharmacological activity of diclofenac sodium gel in reducing inflammation, and possibly fever, may diminish the utility of diagnostic signs in detecting infections.

5.14 Laboratory Monitoring

Because serious GI bleeding, hepatotoxicity, and renal injury can occur without warning symptoms or signs, consider monitoring patients on long-term NSAID treatment with a CBC and a chemistry profile periodically [see Warnings and Precautions (5.5, 5.6, 5.9)] .

5.15 Photosensitivity

Patients should minimize or avoid exposure to natural or artificial sunlight (tanning beds or UVA/B treatment) while using diclofenac sodium gel. If patients need to be outdoors while using diclofenac sodium gel, they should wear loose-fitting clothes that protect skin from sun exposure and discuss other sun protection measures with their physician. Advise patients to discontinue treatment with diclofenac sodium gel at the first evidence of sunburn.

5.16 Exposure to Eyes and Mucosal Membranes

Avoid contact of diclofenac sodium gel with eyes and mucosa. Advise patients that if contact in the eye, or mucosal membranes occurs, immediately wash out the eye or mucosal membranes with water or saline and consult a physician if irritation persists for more than an hour.

5.17 Oral Nonsteroidal Anti-inflammatory Drugs

Concomitant use of oral and topical NSAIDs may result in a higher rate of hemorrhage, more frequent abnormal creatinine, urea and hemoglobin. Do not use diclofenac sodium gel in combination with an oral NSAID unless the benefit outweighs the risk and periodic laboratory evaluations are conducted.

6 ADVERSE REACTIONS

The following adverse reactions are discussed in greater detail in other sections of the labeling:

- Anaphylactic Reactions [see Warnings and Precautions (5.1)]
- Exacerbation of Asthma Related to Aspirin Sensitivity [see Warnings and Precautions (5.2)]
- Serious Skin Reactions [see Warnings and Precautions (5.3)]
- Cardiovascular Thrombotic Events [see Warnings and Precautions (5.4)]
- GI Bleeding, Ulceration and Perforation [see Warnings and Precautions (5.5)]
- Hepatotoxicity [see Warnings and Precautions (5.6)]
- Hypertension [see Warnings and Precautions (5.7)]
- Heart Failure and Edema [see Warnings and Precautions (5.8)]
- Renal Toxicity and Hyperkalemia [see Warnings and Precautions (5.9)]
- DRESS [see Warnings and Precautions (5.10)]
- Hematologic Toxicity [see Warnings and Precautions (5.12)]
- Photosensitivity [see Warnings and Precautions (5.15)]

6.1 Clinical Trials Experience

Because clinical trials are conducted under widely varying conditions, adverse reaction rates observed in the clinical trials of a drug cannot be directly compared to rates in the clinical trials of another drug and may not reflect the rates observed in practice.

Of the 423 subjects evaluable for safety in adequate and well-controlled trials, 211 were treated with diclofenac sodium gel drug product and 212 were treated with a vehicle gel. Eighty-seven percent (87%) of the diclofenac sodium gel-treated subjects (183 subjects) and 84% of the vehicle-treated subjects (178 subjects) experienced one or more adverse events (AEs) during the trials. The majority of these reactions were mild to moderate in severity and resolved upon discontinuation of therapy.

Of the 211 subjects treated with diclofenac sodium gel, 172 (82%) experienced AEs involving skin and the application site compared to 160 (75%) vehicle-treated subjects. Application site reactions (ASRs) were the most frequent AEs in both diclofenac sodium gel-and vehicle-treated groups. Of note, four reactions, contact dermatitis, rash, dry skin and exfoliation(scaling) were significantly more prevalent in the diclofenac sodium gel group than in the vehicle-treated subjects.

Eighteen percent of diclofenac sodium gel-treated subjects and 4% of vehicle-treated subjects discontinued from the clinical trials due to adverse events (whether considered related to treatment or not). These discontinuations were mainly due to skin irritation or related cutaneous adverse reactions.

Table 1 below presents the AEs reported at an incidence of >1% for subjects treated with either diclofenac sodium gel or vehicle (60- and 90-day treatment groups) during the phase 3 trials.

Table 1. Adverse Events Reported (>1% in Any Treatment Group) During Diclofenac Sodium Gel Phase 3 Clinical Trials Incidences for 60-Day and 90-Day Treatments

 | 60-day Treatment |  | 90-day Treatment
 | Diclofenac Sodium Gel (%) | Gel Vehicle (%) | Diclofenac Sodium Gel (%) | Gel Vehicle (%)
 | N=48 | N=49 | N=114 | N=114
- BODY AS A WHOLE | 21 | 20 | 20 | 18
- Abdominal Pain | 2 | 0 | 1 | 0
- Accidental Injury | 0 | 0 | 4 | 2
- Allergic Reaction | 0 | 0 | 1 | 3
- Asthenia | 0 | 0 | 2 | 0
- Back Pain | 4 | 0 | 2 | 2
- Chest Pain | 2 | 0 | 1 | 0
- Chills | 0 | 2 | 0 | 0
- Flu Syndrome | 10 | 6 | 1 | 4
- Headache | 0 | 6 | 7 | 6
- Infection | 4 | 6 | 4 | 5
- Neck Pain | 0 | 0 | 2 | 0
- Pain | 2 | 0 | 2 | 2
- CARDIOVASCULAR SYSTEM | 2 | 4 | 3 | 1
- Hypertension | 2 | 0 | 1 | 0
- Migraine | 0 | 2 | 1 | 0
- Phlebitis | 0 | 2 | 0 | 0
- DIGESTIVE SYSTEM | 4 | 0 | 6 | 8
- Constipation | 0 | 0 | 0 | 2
- Diarrhea | 2 | 0 | 2 | 3
- Dyspepsia | 2 | 0 | 3 | 4
- METABOLIC AND NUTRITIONAL DISORDERS | 2 | 8 | 7 | 2
- Creatine Phosphokinase Increased | 0 | 0 | 4 | 1
- Creatinine Increased | 2 | 2 | 0 | 1
- Edema | 0 | 2 | 0 | 0
- Hypercholesteremia | 0 | 2 | 1 | 0
- Hyperglycemia | 0 | 2 | 1 | 0
- SGOT Increased | 0 | 0 | 3 | 0
- SGPT Increased | 0 | 0 | 2 | 0
- MUSCULOSKELETAL SYSTEM | 4 | 0 | 3 | 4
- Arthralgia | 2 | 0 | 0 | 2
- Arthrosis | 2 | 0 | 0 | 0
- Myalgia | 2 | 0 | 3 | 1
- NERVOUS SYSTEM | 2 | 2 | 2 | 5
- Anxiety | 0 | 2 | 0 | 1
- Dizziness | 0 | 0 | 0 | 4
- Hypokinesia | 2 | 0 | 0 | 0
- RESPIRATORY SYSTEM | 8 | 8 | 7 | 6
- Asthma | 2 | 0 | 0 | 0
- Dyspnea | 2 | 0 | 2 | 0
- Pharyngitis | 2 | 8 | 2 | 4
- Pneumonia | 2 | 0 | 0 | 1
- Rhinitis | 2 | 2 | 2 | 2
- Sinusitis | 0 | 0 | 2 | 0
- SKIN AND APPENDAGES | 75 | 86 | 86 | 71
- Acne | 0 | 2 | 0 | 1
- Application Site Reaction | 75 | 71 | 84 | 70
- Acne | 0 | 4 | 1 | 0
- Alopecia | 2 | 0 | 1 | 1
- Contact Dermatitis | 19 | 4 | 33 | 4
- Dry Skin | 27 | 12 | 25 | 17
- Edema | 4 | 0 | 3 | 0
- Exfoliation | 6 | 4 | 24 | 13
- Hyperesthesia | 0 | 0 | 3 | 1
- Pain | 15 | 22 | 26 | 30
- Paresthesia | 8 | 4 | 20 | 20
- Photosensitivity Reaction | 0 | 2 | 3 | 0
- Pruritus | 31 | 59 | 52 | 45
- Rash | 35 | 20 | 46 | 17
- Vesiculobullous Rash | 0 | 0 | 4 | 1
- Contact Dermatitis | 2 | 0 | 0 | 0
- Dry Skin | 0 | 4 | 3 | 0
- Herpes Simplex | 0 | 2 | 0 | 0
- Maculopapular Rash | 0 | 2 | 0 | 0
- Pain | 2 | 2 | 1 | 0
- Pruritus | 4 | 6 | 4 | 1
- Rash | 2 | 10 | 4 | 0
- Skin Carcinoma | 0 | 6 | 2 | 2
- Skin Nodule | 0 | 2 | 0 | 0
- Skin Ulcer | 2 | 0 | 1 | 0
- SPECIAL SENSES | 2 | 0 | 4 | 2
- Conjunctivitis | 2 | 0 | 4 | 1
- Eye Pain | 0 | 2 | 2 | 0
- UROGENITAL SYSTEM | 0 | 0 | 4 | 5
- Hematuria | 0 | 0 | 2 | 1
- OTHER | 0 | 0 | 0 | 3
- Procedure | 0 | 0 | 0 | 3

Skin and Appendages Adverse Events Reported for Diclofenac Sodium Gel at Less Than 1% Incidence in the Phase 3 Studies:skin hypertrophy, paresthesia, seborrhea, urticaria, application site reactions (skin carcinoma, hypertonia, skin hypertrophy lacrimation disorder, maculopapular rash, purpuric rash, vasodilation).

Adverse Reactions Reported for OralDiclofenac Dosage Form (not topical diclofenac sodium gel): *Incidence Greater than 1% marked with asterisk.

Body as a Whole:abdominal pain or cramps*, headache*, fluid retention*, abdominal distention*, malaise, swelling of lips and tongue, photosensitivity, anaphylaxis, anaphylactoid reactions, chest pain.

Cardiovascular:hypertension, congestive heart failure, palpitations, flushing, tachycardia, premature ventricular contractions, myocardial infarction, hypotension.

Digestive:diarrhea*, indigestion*, nausea*, constipation*, flatulence*, liver test abnormalities*, PUB*, i.e., peptic ulcer, with or without bleeding and/or perforation, or bleeding without ulcer, vomiting, jaundice, melena, esophageal lesions, aphthous stomatitis, dry mouth and mucous membranes, bloody diarrhea, hepatitis, hepatic necrosis, cirrhosis, hepatorenal syndrome, appetite change, pancreatitis with or without concomitant hepatitis, colitis, intestinal perforation.

Hemic and Lymphatic:hemoglobin decrease, leukopenia, thrombocytopenia, eosinophilia, hemolytic anemia, aplastic anemia, agranulocytosis, purpura, allergic purpura, bruising.

Metabolic and Nutritional Disorders:azotemia, hypoglycemia, weight loss.

Nervous System:dizziness*, insomnia, drowsiness, depression, diplopia, anxiety, irritability, aseptic meningitis, convulsions, paresthesia, memory disturbance, nightmares, tremor, tic, abnormal coordination, disorientation, psychotic reaction.

Respiratory:epistaxis, asthma, laryngeal edema, dyspnea, hyperventilation, edema of pharynx.

Skin and Appendages:rash*, pruritus*, alopecia, urticaria, eczema, dermatitis, bullous eruption, erythema multiforme major, angioedema, Stevens-Johnson syndrome, excess perspiration, exfoliative dermatitis.

Special Senses:tinnitus*, blurred vision, taste disorder, reversible and irreversible hearing loss, scotoma, vitreous floaters, night blindness, amblyopia.

Urogenital:nephrotic syndrome, proteinuria, oliguria, interstitial nephritis, papillary necrosis, acute renal failure, urinary frequency, nocturia, hematuria, impotence, vaginal bleeding.

6.2 Postmarketing Experience

The following adverse reactions have been identified during post-approval use of diclofenac sodium gel and other topical diclofenac products. Because these reactions are reported voluntarily from a population of uncertain size, it is not always possible to reliably estimate their frequency or establish a causal relationship to drug exposure.

Adverse reactions from diclofenac sodium gel: burning sensation, hypersensitivity.

Adverse reactions from other topical diclofenac products: hypoesthesia, gait disturbance, musculoskeletal stiffness.

7 DRUG INTERACTIONS

See Table 2 for clinically significant drug interactions with diclofenac.

Table 2: Clinically Significant Drug Interactions with Diclofenac

Drugs That Interfere with Hemostasis
Clinical Impact: | - Diclofenac and anticoagulants such as warfarin have a synergistic effect on bleeding. The concomitant use of diclofenac and anticoagulants have an increased risk of serious bleeding compared to the use of either drug alone. - Serotonin release by platelets plays an important role in hemostasis. Case-control and cohort epidemiological studies showed that concomitant use of drugs that interfere with serotonin reuptake and an NSAID may potentiate the risk of bleeding more than an NSAID alone.
Intervention: | - Monitor patients with concomitant use of diclofenac sodium gel with anticoagulants (e.g., warfarin), antiplatelet agents (e.g., aspirin), selective serotonin reuptake inhibitors (SSRIs), and serotonin norepinephrine reuptake inhibitors (SNRIs) for signs of bleeding [see Warnings and Precautions (5.5)] .
Aspirin
Clinical Impact: | - In a clinical study, the concomitant use of an NSAID and aspirin was associated with a significantly increased incidence of GI adverse reactions as compared to use of the NSAID alone [see Warnings and Precautions (5.5)] .
Intervention: | - Concomitant use of diclofenac sodium gel and analgesic doses of aspirin is not generally recommended because of the increased risk of bleeding [see Warnings and Precautions (5.12)] . Diclofenac sodium gel is not a substitute for low dose aspirin for cardiovascular protection.
ACE Inhibitors, Angiotensin Receptor Blockers, and Beta-Blockers
Clinical Impact: | - NSAIDs may diminish the antihypertensive effect of angiotensin converting enzyme (ACE) inhibitors, angiotensin receptor blockers (ARBs), or beta-blockers (including propranolol). - In patients who are elderly, volume-depleted (including those on diuretic therapy), or have renal impairment, co-administration of an NSAID with ACE inhibitors or ARBs may result in deterioration of renal function, including possible acute renal failure. These effects are usually reversible.
Intervention: | - During concomitant use of diclofenac sodium gel and ACE-inhibitors, ARBs, or beta-blockers, monitor blood pressure to ensure that the desired blood pressure is obtained. - During concomitant use of diclofenac sodium gel and ACE-inhibitors or ARBs in patients who are elderly, volume-depleted, or have impaired renal function, monitor for signs of worsening renal function [see Warnings and Precautions (5.9)] .
Diuretics
Clinical Impact: | - Clinical studies, as well as post-marketing observations, showed that NSAIDs reduced the natriuretic effect of loop diuretics (e.g., furosemide) and thiazide diuretics in some patients. This effect has been attributed to the NSAID inhibition of renal prostaglandin synthesis.
Intervention: | - During concomitant use of diclofenac sodium gel with diuretics, observe patients for signs of worsening renal function, in addition to assuring diuretic efficacy including antihypertensive effects [see Warnings and Precautions (5.9)] .
Digoxin
Clinical Impact: | - The concomitant use of diclofenac with digoxin has been reported to increase the serum concentration and prolong the half-life of digoxin.
Intervention: | - During concomitant use of diclofenac sodium gel and digoxin, monitor serum digoxin levels.
Lithium
Clinical Impact: | - NSAIDs have produced elevations in plasma lithium levels and reductions in renal lithium clearance. The mean minimum lithium concentration increased 15%, and the renal clearance decreased by approximately 20%. This effect has been attributed to NSAID inhibition of renal prostaglandin synthesis.
Intervention: | - During concomitant use of diclofenac sodium gel and lithium, monitor patients for signs of lithium toxicity.
Methotrexate
Clinical Impact: | - Concomitant use of NSAIDs and methotrexate may increase the risk for methotrexate toxicity (e.g., neutropenia, thrombocytopenia, renal dysfunction).
Intervention: | - During concomitant use of diclofenac sodium gel and methotrexate, monitor patients for methotrexate toxicity.
Cyclosporine
Clinical Impact: | - Concomitant use of diclofenac sodium gel and cyclosporine may increase cyclosporine’s nephrotoxicity.
Intervention: | - During concomitant use of diclofenac sodium gel and cyclosporine, monitor patients for signs of worsening renal function.
NSAIDs and Salicylates
Clinical Impact: | - Concomitant use of diclofenac sodium gel with other NSAIDs or salicylates (e.g., diflunisal, salsalate) increases the risk of GI toxicity [see Warnings and Precautions (5.5)] .
Intervention: | - The concomitant use of diclofenac sodium gel with other NSAIDs or salicylates is not recommended.
Pemetrexed
Clinical Impact: | - Concomitant use of diclofenac sodium gel and pemetrexed may increase the risk of pemetrexed-associated myelosuppression, renal, and GI toxicity (see the pemetrexed prescribing information).
Intervention: | - During concomitant use of diclofenac sodium gel and pemetrexed, in patients with renal impairment whose creatinine clearance ranges from 45 to 79 mL/min, monitor for myelosuppression, renal and GI toxicity. NSAIDs with short elimination half-lives (e.g., diclofenac, indomethacin) should be avoided for a period of two days before, the day of, and two days following administration of pemetrexed. In the absence of data regarding potential interaction between pemetrexed and NSAIDs with longer half-lives (e.g., meloxicam, nabumetone), patients taking these NSAIDs should interrupt dosing for at least five days before, the day of, and two days following pemetrexed administration.

8 USE IN SPECIFIC POPULATIONS

8.1 Pregnancy

Risk Summary

Use of NSAIDs, including diclofenac sodium gel, can cause premature closure of the fetal ductus arteriosus and fetal renal dysfunction leading to oligohydramnios and, in some cases, neonatal renal impairment. Because of these risks, limit dose and duration of diclofenac sodium gel use between about 20 and 30 weeks of gestation and avoid diclofenac sodium gel use at about 30 weeks of gestation and later in pregnancy.

Oligohydramnios/Neonatal Renal Impairment

Use of NSAIDs at about 20 weeks gestation or later in pregnancy has been associated with cases of fetal renal dysfunction leading to oligohydramnios, and in some cases, neonatal renal impairment.

Premature Closure of Fetal Ductus Arteriosus

Use of NSAIDs, including diclofenac sodium gel, at about 30 weeks gestation or later in pregnancy increases the risk of premature closure of the fetal ductus arteriosus.

Data from observational studies regarding other potential embryofetal risks of NSAID use in women in the first or second trimesters of pregnancy are inconclusive.

In animal reproduction studies, no evidence of malformations was observed in mice, rats, or rabbits given diclofenac during the period of organogenesis at doses at least 15 times, the maximum recommended human dose (MRHD) of diclofenac sodium gel (see Data). Based on published animal data, prostaglandins have been shown to have an important role in endometrial vascular permeability, blastocyst implantation, and decidualization, and administration of prostaglandin synthesis inhibitors such as diclofenac sodium, resulted in increased pre- and post-implantation loss. Prostaglandins also have been shown to have an important role in fetal kidney development. In published animal studies, prostaglandin synthesis inhibitors have been reported to impair kidney development when administered at clinically relevant doses.

The background risk of major birth defects and miscarriage for the indicated population(s) is unknown. All pregnancies have a background risk of birth defect, loss, or other adverse outcomes. In the U.S. general population, the estimated background risk of major birth defects and miscarriage in clinically recognized pregnancies is 2% to 4% and 15% to 20%, respectively.

Clinical Considerations

Fetal/Neonatal Adverse Reactions

Premature Closure of Fetal Ductus Arteriosus

Avoid use of NSAIDs in women at about 30 weeks gestation and later in pregnancy, because NSAIDs, including diclofenac sodium gel, can cause premature closure of the fetal ductus arteriosus.

Oligohydramnios/Neonatal Renal Impairment

If after careful consideration of alternative treatment options for actinic keratoses, an NSAID is necessary at about 20 weeks gestation or later in pregnancy, limit the use to the lowest effective dose and shortest duration possible. If diclofenac sodium gel treatment extends beyond 48 hours, consider monitoring with ultrasound for oligohydramnios. If oligohydramnios occurs, discontinue diclofenac sodium gel and follow up according to clinical practice.

Labor or Delivery

There are no studies on the effects of diclofenac sodium gel during labor or delivery. In animal studies, NSAIDS, including diclofenac, inhibit prostaglandin synthesis, cause delayed parturition, and increase the incidence of stillbirth.

Data

Human Data

Premature Closure of Fetal Ductus Arteriosus

Published literature reports that the use of NSAIDs at about 30 weeks of gestation and later in pregnancy may cause premature closure of the fetal ductus arteriosus.

Oligohydramnios/Neonatal Renal Impairment

Published studies and postmarketing reports describe maternal NSAID use at about 20 weeks gestation or later in pregnancy associated with fetal renal dysfunction leading to oligohydramnios, and in some cases, neonatal renal impairment. These adverse outcomes are seen, on average, after days to weeks of treatment, although oligohydramnios has been infrequently reported as soon as 48 hours after NSAID initiation. In many cases, but not all, the decrease in amniotic fluid was transient and reversible with cessation of the drug. There have been a limited number of case reports of maternal NSAID use and neonatal renal dysfunction without oligohydramnios, some of which were irreversible. Some cases of neonatal renal dysfunction required treatment with invasive procedures, such as exchange transfusion or dialysis.

Methodological limitations of these postmarketing studies and reports include lack of a control group; limited information regarding dose, duration, and timing of drug exposure; and concomitant use of other medications. These limitations preclude establishing a reliable estimate of the risk of adverse fetal and neonatal outcomes with maternal NSAID use.

Because the published safety data on neonatal outcomes involved mostly preterm infants, the generalizability of certain reported risks to the full-term infant exposed to NSAIDs through maternal use is uncertain.

Animal Data

The multiples provided in this labeling are based on an MRHD that assumes 10% bioavailability following topical application of 2 g diclofenac sodium gel per day (1 mg/kg diclofenac sodium).

Reproductive studies performed with diclofenac sodium alone at oral doses up to 20 mg/kg/day (15 times the MRHD based on body surface area (BSA) comparisons) in mice, 10 mg/kg/day (15 times the MRHD based on BSA comparisons) in rats, and 10 mg/kg/day (30 times the MRHD based on BSA comparisons) in rabbits have revealed no evidence of malformations despite the induction of maternal toxicity. In rats, maternally toxic doses were associated with dystocia, prolonged gestation, reduced fetal weights and growth, and reduced fetal survival. Diclofenac has been shown to cross the placental barrier in mice and rats.

8.2 Lactation

Risk Summary

Data from published literature cases with oral preparations of diclofenac indicate the presence of small amounts of diclofenac in human milk. There are no data on the effects on the breastfed infant, or the effects on milk production. The developmental and health benefits of breastfeeding should be considered along with the mother’s clinical need for diclofenac sodium gel and any potential adverse effects on the breastfed infant from the diclofenac sodium gel or from the underlying maternal condition.

Data

One woman treated orally with a diclofenac salt, 150 mg/day, had a milk diclofenac level of 100 mcg/L, equivalent to an infant dose of about 0.03 mg/kg/day. Diclofenac was not detectable in breast milk in 12 women using diclofenac (after either 100 mg/day orally for 7 days or a single 50 mg intramuscular dose administered in the immediate postpartum period). The systemic bioavailability after topical application of diclofenac sodium gel is lower than after oral dosing [see Clinical Pharmacology (12.3)] .

8.3 Females and Males of Reproductive Potential

Female Infertility

Based on the mechanism of action, the use of prostaglandin mediated NSAIDs, including diclofenac sodium gel, may delay or prevent rupture of ovarian follicles, which has been associated with reversible infertility in some women [see Clinical Pharmacology (12.1)] .

Published animal studies have shown that administration of prostaglandin synthesis inhibitors has the potential to disrupt prostaglandin-mediated follicular rupture required for ovulation. Small studies in women treated with NSAIDs have also shown a reversible delay in ovulation. Consider withdrawal of NSAIDs, including diclofenac sodium gel, in women who have difficulties conceiving or who are undergoing investigation of infertility.

8.4 Pediatric Use

Actinic keratoses is not a condition seen within the pediatric population. diclofenac sodium gel should not be used by children.

8.5 Geriatric Use

Elderly patients, compared to younger patients, are at greater risk for NSAID-associated serious cardiovascular, gastrointestinal, and/or renal adverse reactions. If the anticipated benefit for the elderly patient outweighs these potential risks, start dosing at the low end of the dosing range, and monitor patients for adverse effects [see Warnings and Precautions (5.4, 5.5, 5.6, 5.9, 5.14)].

Of the 211 subjects treated with diclofenac sodium gel in controlled clinical trials, 143 subjects were 65 years of age and over. Of those 143 subjects, 55 subjects were 75 years of age and over. No overall differences in safety or effectiveness were observed between these subjects and younger subjects, and other reported clinical experience has not identified differences in responses between the elderly and younger patients, but greater sensitivity of some older individuals cannot be ruled out.

10 OVERDOSAGE

Symptoms following acute NSAID overdosages have been typically limited to lethargy, drowsiness, nausea, vomiting, and epigastric pain, which have been generally reversible with supportive care. Gastrointestinal bleeding, hypertension, acute renal failure, respiratory depression, and coma have been reported. [see Warnings and Precautions (5.4, 5.5, 5.7, 5.9)] .

Manage patients with symptomatic and supportive care following an NSAID overdosage. There are no specific antidotes. Forced diuresis, alkalinization of urine, hemodialysis, or hemoperfusion may not be useful due to high protein binding.

In the event of oral ingestion, resulting in significant systemic side effects, it is recommended that the stomach be emptied by vomiting or lavage. In addition to supportive measures, the use of oral activated charcoal may help to reduce the absorption of diclofenac.

For additional information about overdosage treatment, call a poison control center (1-800-222-1222).

11 DESCRIPTION

Diclofenac Sodium Topical Gel, 3%, intended for dermatologic use, contains the active ingredient, diclofenac sodium, USP in a clear, transparent, colorless to slightly yellow gel base. Diclofenac sodium, USP is a white to slightly yellowish, hygroscopic crystalline powder, and melts at about 284°C. It is freely soluble in methanol, soluble in ethanol, sparingly soluble in water, slightly soluble in acetone, and partially insoluble in chloroform and ether. The chemical name for diclofenac sodium is:

Sodium [ o-(2,6-dichloranilino) phenyl] acetate

Diclofenac sodium has a molecular weight of 318.13.

The CAS number is CAS-15307-79-6. The structural formula is represented below:

Diclofenac Sodium Gel, 3% also contains benzyl alcohol, sodium hyaluronate, polyethylene glycol monomethyl ether, and purified water.

1 g of Diclofenac Sodium Topical Gel, 3% contains 30 mg of the active substance, diclofenac sodium, USP.

12 CLINICAL PHARMACOLOGY

12.1 Mechanism of Action

The mechanism of action of diclofenac sodium in the treatment of actinic keratoses (AK) is unknown.

12.2 Pharmacodynamics

The pharmacodynamics of diclofenac sodium gel in the treatment of actinic keratosis has not been assessed.

12.3 Pharmacokinetics

Absorption

Diclofenac levels were measured at the end of treatment from 60 patients with AK lesions treated with diclofenac sodium gel in three adequate and well-controlled clinical trials. Each patient was administered 0.5 g of diclofenac sodium gel twice a day for up to 105 days. There were up to three 5 cm x 5 cm treatment sites per patient on the face, forehead, hands, forearm, and scalp. Serum concentrations of diclofenac were, on average, at or below 20 ng/mL.

Distribution

Diclofenac binds tightly to serum albumin.

Metabolism

Biotransformation of diclofenac following oral administration involves conjugation at the carboxyl group of the side chain or single or multiple hydroxylations resulting in several phenolic metabolites, most of which are converted to glucuronide conjugates. Two of these phenolic metabolites are biologically active, however to a much smaller extent than diclofenac. Metabolism of diclofenac following topical administration is thought to be similar to that after oral administration. The small amounts of diclofenac and its metabolites appearing in the plasma following topical administration makes the quantification of specific metabolites imprecise.

Elimination

Diclofenac and its metabolites are excreted mainly in the urine after oral dosing.

13 NONCLINICAL TOXICOLOGY

13.1 Carcinogenesis, Mutagenesis, Impairment of Fertility

There did not appear to be any increase in drug-related neoplasms following daily topical applications of diclofenac sodium gel for 2 years at concentrations up to 0.035% diclofenac sodium and 2.5% hyaluronate sodium in albino mice.

When administered orally for 2 years, diclofenac showed no evidence of carcinogenic potential in rats given diclofenac sodium at up to 2 mg/kg/day (3 times the MRHD based on BSA comparison), or in mice given diclofenac sodium at up to 0.3 mg/kg/day in males and 1 mg/kg/day in females (25% and 83%, respectively, of the MRHD based on BSA comparison).

Diclofenac was not genotoxic in in vitropoint mutation assays in mammalian mouse lymphoma cells and Ames microbial test systems, or when tested in mammalian in vivoassays including dominant lethal and male germinal epithelial chromosomal studies in mice, and nucleus anomaly and chromosomal aberration studies in Chinese hamsters. It was also negative in the transformation assay utilizing BALB/3T3 mouse embryo cells.

Fertility studies have not been conducted with diclofenac sodium gel. Diclofenac sodium showed no evidence of impairment of fertility after oral treatment with 4 mg/kg/day (7 times the MRHD based on BSA comparison) in male or female rats.

14 CLINICAL STUDIES

Clinical trials were conducted involving a total of 427 patients (213 treated with diclofenac sodium gel and 214 with a gel vehicle). Each patient had no fewer than five AK lesions in a major body area, which was defined as one of five 5 cm x 5 cm regions: scalp, forehead, face, forearm and hand. Up to three major body areas were studied in any patient. All patients were 18 years of age or older (male and female) with no clinically significant medical problems outside of the AK lesions and had undergone a 60-day washout period from disallowed medications (masoprocol, 5-fluorouracil, cyclosporine, retinoids, trichloroacetic acid/lactic acid/peel, 50% glycolic acid peel) and hyaluronan-containing cosmetics. Patients were excluded from participation for reasons of known or suspected hypersensitivity to any diclofenac sodium gel ingredient, pregnancy, allergies to aspirin or other nonsteroidal anti-inflammatory drugs (NSAIDs), or other dermatological conditions which might affect the absorption of the study medication. Application of dermatologic products such as sunscreens, cosmetics, and other drug products was not permitted. Patients were instructed to apply a small amount of diclofenac sodium gel (approximately 0.5 g) onto the affected skin, using their fingers, and gently smoothing the gel over the lesion. In addition, all patients were instructed to avoid sun exposure. Complete clearing of the AK lesions 30 days after completion of treatment was the primary efficacy variable. No long-term patient follow-ups, after the 30-day assessments, were performed for the detection of recurrence.

- Complete Clearance of Actinic Keratosis Lesions 30 Days Post-Treatment (all locations)
 | - Diclofenac Sodium Gel | - Vehicle | - p-value
- Study 1 90 days treatment | - 27/58 (47%) | - 11/59 (19%) | - <0.001
- Study 2 90 days treatment | - 18/53 (34%) | - 10/55 (18%) | - 0.061
- Study 3 60 days treatment | - 15/48 (31%) | - 5/49 (10%) | - 0.021
- 30 days treatment | - 7/49 (14%) | - 2/49 (4%) | - 0.221

Complete Clearance of Actinic Keratosis Lesions 30 Days Post-Treatment (by location)
 | Scalp | Forehead | Face | Arm/Forearm | Back of Hand
Study 1; 90 days; treatment
- Diclofenac Sodium Gel | - 1/4 (25%) | - 17/30 (57%) | - 9/17 (53%) | - 4/12 (33%) | - 6/16 (38%)
- Vehicle | - 3/9 (33%) | - 8/24 (33%) | - 5/17 (29%) | - 4/12 (33%) | - 0/14 (0)
- p-value | - 0.7646 | - 0.0908 | - 0.1682 | - 1.000 | - 0.0650
Study 2; 90 days; treatment
- Diclofenac Sodium Gel | - 2/6 (33%) | - 9/19 (47%) | - 4/5 (80%) | - 5/8 (63%) | - 1/17 (6%)
- Vehicle | - 0/4 (0) | - 6/22 (27%) | - 2/8 (25%) | - 0/5 (0) | - 3/16 (19%)
- p-value | - 0.4235 | - 0.1870 | - 0.0727 | - 0.0888 | - 0.2818
Study 3; 60 days; treatment
- Diclofenac Sodium Gel | - 3/7 (43%) | - 13/31 (42%) | 10/19 (53%) | - 0/1 (0) | - 2/8 (25%)
- Vehicle | - 0/6 (0) | - 5/36 (14%) | - 2/13 (15%) | - 0/2 (0) | - 1/9 (11%)
- p-value | - 0.2271 | - 0.0153 | - 0.0433 | - - | - 0.4637
Study 3; 30 days; treatment
- Diclofenac Sodium Gel | - 2/5 (40%) | - 4/29 (14%) | - 3/14 (21%) | - 0/0 (0) | - 0/9 (0)
- Vehicle | - 0/5 (0) | - 2/29 (7%) | - 2/18 (11%) | - 0/1 (0) | - 1/9 (11%)
- p-value | - 0.2299 | - 0.3748 | - 0.4322 | - - | - 0.6521
All data; combined
- Diclofenac Sodium Gel | - 8/22 (36%) | - 43/109 (39%) | 26/55 (47) | - 9/21 (43%) | - 9/50 (18%)
- Vehicle | - 3/24 (13%) | - 21/111 (19%) | 11/56 (20) | - 4/20 (20%) | - 5/48 (10%)
- p-value | - 0.0903 | - 0.0013 | - 0.0016 | - 0.2043 | - 0.3662

16 HOW SUPPLIED/STORAGE AND HANDLING

Each gram of Diclofenac Sodium Topical Gel, 3% contains 30 mg of diclofenac sodium, USP. Diclofenac Sodium Gel, 3% is available as follows:

1. NDC 68071-3516-1 100 g tube (1 tube per carton)

Storage:Store at 20°C to 25°C (68°F to 77°F); excursions permitted between 15°C to 30°C (59°F to 86°F) [see USP Controlled Room Temperature]. Protect from heat. Avoid freezing.

17 PATIENT COUNSELING INFORMATION

Advise the patient to read the FDA-approved patient labeling (Medication Guide) that accompanies each prescription dispensed, as well as the Directions for Use on the product packaging. Inform patients, families, or their caregivers of the following information before initiating therapy with diclofenac sodium gel and periodically during the course of ongoing therapy.

Special Application Instructions

- Instruct patients not to apply diclofenac sodium gel to damaged skin resulting from any etiology, e.g., exudative dermatitis, eczema, infected lesion, burns or wounds.
- Instruct patients to minimize or avoid exposure to natural or artificial sunlight (tanning beds or UVA/B treatment) while using diclofenac sodium gel. If patients need to be outdoors while using diclofenac sodium gel, they should wear loose-fitting clothes that protect skin from sun exposure and discuss other sun protection measures with their physician. Advise patients to discontinue treatment with diclofenac sodium gel at the first evidence of sunburn.

Anaphylactic Reactions

Inform patients of the signs of an anaphylactic reaction (e.g., difficulty breathing, swelling of the face or throat). Instruct patients to seek immediate emergency help if these occur [see Contraindications (4) and Warnings and Precautions (5.1)] .

Exacerbation of Asthma Related to Aspirin Sensitivity

Inform patients with aspirin sensitive asthma not to use diclofenac sodium gel. Advise patients with preexisting asthma to report any changes in the signs and symptoms of asthma to their healthcare provider [see Contraindications (4) and Warnings and Precautions (5.2)] .

Serious Skin Reactions including DRESS

Advise patients to stop using diclofenac sodium gel immediately if they develop any type of rash or fever and to contact their healthcare provider as soon as possible [see Warnings and Precautions (5.3, 5.10)] .

Cardiovascular Thrombotic Events

Advise patients to be alert for the symptoms of cardiovascular thrombotic events, including chest pain, shortness of breath, weakness, or slurring of speech, and to report any of these symptoms to their health care provider immediately [see Warnings and Precautions (5.4)] .

Gastrointestinal Bleeding, Ulceration, and Perforation

Advise patients to report symptoms of ulcerations and bleeding, including epigastric pain, dyspepsia, melena, and hematemesis to their health care provider. In the setting of concomitant use of low-dose aspirin for cardiac prophylaxis, inform patients of the increased risk for and the signs and symptoms of GI bleeding [see Warnings and Precautions (5.5)] .

Hepatotoxicity

Inform patients of the warning signs and symptoms of hepatotoxicity (e.g., nausea, fatigue, lethargy, pruritus, diarrhea, jaundice, right upper quadrant tenderness, and “flu-like” symptoms). Inform the patient that diclofenac sodium gel may increase the risk of elevated liver enzymes. Advise the patient that laboratory evaluation is needed prior to and periodically during treatment. Advise the patient that if signs or symptoms of liver injury occur, discontinue diclofenac sodium gel and seek medical advice promptly [see Warnings and Precautions (5.6)] .

Heart Failure and Edema

Advise patients to be alert for the symptoms of congestive heart failure including shortness of breath, unexplained weight gain, or edema and to contact their healthcare provider if such symptoms occur [see Warnings and Precautions (5.8)] .

Female Fertility

Advise females of reproductive potential who desire pregnancy that NSAIDs, including diclofenac sodium gel, may be associated with reversible delay in ovulation [see Use in Specific Populations (8.3)] .

Fetal Toxicity

Inform pregnant women to avoid use of diclofenac sodium gel and other NSAIDs starting at 30 weeks gestation because of the risk of the premature closing of the fetal ductus arteriosus. If treatment with diclofenac sodium gel is needed for a pregnant woman between about 20 to 30 weeks gestation, advise her that she may need to be monitored for oligohydramnios, if treatment continues for longer than 48 hours [see Warnings and Precautions (5.11) and Use in Specific Populations (8.1)] .

Avoid Concomitant Use of NSAIDs

Inform patients that the concomitant use of diclofenac sodium gel with other NSAIDs or salicylates (e.g., diflunisal, salsalate) is not recommended due to the increased risk of gastrointestinal toxicity [see Warnings and Precautions (5.5)andDrug Interactions (7)] . Alert patients that NSAIDs may be present in “over the counter” medications for treatment of colds, fever, or insomnia.

Use of NSAIDS and Low-Dose Aspirin

Inform patients not to use low-dose aspirin concomitantly with diclofenac sodium gel until they talk to their healthcare provider [see Drug Interactions (7)] .

Exposure to Eyes and Mucosal Membranes

Instruct patients to avoid contact of diclofenac sodium gel with the eyes and mucosal membranes. Advise patients that if eye or mucosal membrane contact occurs, immediately wash out with water or saline and consult a physician if irritation persists for more than an hour [see Warnings and Precautions (5.16)] .

Trademarks are the property of their respective owners.

Medication Guide available at

www.glenmarkpharma-us.com/medguides

Manufactured by:

Glenmark Pharmaceuticals Limited

Colvale-Bardez, Goa 403513, India

Manufactured for:

Glenmark Pharmaceuticals Inc., USA

Mahwah, NJ 07430

Questions? 1 (888) 721-7115

www.glenmarkpharma-us.com

July 2023

Medication Guide

Dispense with Medication Guide available at:

www.glenmarkpharma-us.com/medguides

- Diclofenac Sodium (dye-KLOE-fen-ak SOE-dee-um)
  Gel

What is the most important information I should know about diclofenac sodium gel and medicines called Nonsteroidal Anti-inflammatory Drugs (NSAIDs)?

NSAIDs can cause serious side effects, including:

- Increased risk of a heart attack or stroke that can lead to death. This risk may happen early in treatment and may increase:
  - with increasing doses of NSAIDs
  - with longer use of NSAIDs

Do not take or use NSAIDs right before or after a heart surgery called a “coronary artery bypass graft (CABG)”. Avoid taking NSAIDs after a recent heart attack unless your healthcare provider tells you to. You may have an increased risk of another heart attack if you take or use NSAIDs after a recent heart attack.

- Increased risk of bleeding, ulcers, and tears (perforation) of the esophagus (tube leading from the mouth to the stomach), stomach and intestines:
  - anytime during use
  - without warning symptoms
  - that may cause death

The risk of getting an ulcer or bleeding increases with:

- past history of stomach ulcers, or stomach or intestinal bleeding with use of NSAIDs
- taking medicines called “corticosteroids”, “anticoagulants”, “SSRIs”, or “SNRIs”
- increasing doses of NSAIDs
- longer use of NSAIDs
- smoking
- drinking alcohol
- older age
- poor health
- advanced liver disease
- bleeding problems

NSAIDs should only be used:

- exactly as prescribed
- at the lowest dose possible for your treatment
- for the shortest time needed

What is diclofenac sodium gel?

Diclofenac sodium gel is an NSAID that is used on the skin (topical) to treat a skin condition called actinic keratosis. Diclofenac sodium gel is not for use in children.

- Do not use diclofenac sodium gel:

- if you have had an allergic reaction to any of the ingredients in diclofenac sodium gel. See the end of this Medication Guide for a complete list of ingredients in diclofenac sodium gel.
- if you have a history of asthma, hives, or other allergic-type reactions after taking aspirin or other NSAIDs. Severe allergic reactions that can sometimes lead to death, have happened in people with a history of these types of allergic reactions to NSAIDs.
- on skin that is inflamed, or has eczema, infected sores (lesions), burns or wounds
- right before or after heart bypass surgery.

Before using diclofenac sodium gel, tell your healthcare provider about all of your medical conditions, including if you:

- have liver or kidney problems
- have high blood pressure
- have asthma
- are pregnant or plan to become pregnant. Taking NSAIDs at about 20 weeks of pregnancy or later may harm your unborn baby. If you need to take NSAIDs for more than 2 days when you are between 20 and 30 weeks of pregnancy, your healthcare provider may need to monitor the amount of fluid in your womb around your baby. You should not take NSAIDs after about 30 weeks of pregnancy.
- are breastfeeding or plan to breastfeed. You and your healthcare provider should decide if you will use diclofenac sodium gel or breastfeed.

Tell your healthcare provider about all of the medicines you take, including prescription or over-the-counter medicines, vitamins, or herbal supplements.NSAIDs and some other medicines can interact with each other and cause serious side effects. Do not start taking any new medicine without talking to your healthcare provider first.

How should I use diclofenac sodium gel?

- Use diclofenac sodium gel exactly as your healthcare provider tells you to use it.
- Apply diclofenac sodium gel 2 times a day.
- Apply enough diclofenac sodium gel to cover each skin lesion (usually a pea-sized amount) and gently rub in.
- Diclofenac sodium gel may be used for 60 to 90 days. You may not see improvement of skin lesions for up to 30 days after stopping treatment. See your healthcare provider if lesions do not respond to treatment.
- Avoid getting diclofenac sodium gel in your eyes, nose and mouth. If diclofenac sodium gel gets into your eyes, nose or mouth wash out your eyes, nose or mouth with water or saline right away. Call your healthcare provider if irritation continues for more than 1 hour.
- Wash your hands well after applying diclofenac sodium gel.

What should I avoid while using diclofenac sodium gel?

- Avoid spending time in sunlight or artificial light, such as tanning beds or sunlamps. Diclofenac sodium gel can make your skin sensitive to sunlight and the light from tanning beds and sunlamps. Talk to your healthcare provider about sun protection measures and wear loose-fitting clothes that cover your skin while out in sunlight. Stop using diclofenac sodium gel if you notice that you are beginning to get sunburn.
- Do not apply diclofenac sodium gel to open skin wounds, skin infections, or peeling skin.

What are the possible side effects of diclofenac sodium gel?

Diclofenac sodium gel and other NSAIDs can cause serious side effects, including:

See “What is the most important information I should know about diclofenac sodium gel and medicines called Nonsteroidal Anti-inflammatory Drugs (NSAIDs)?

- life threatening allergic reactions
- worsening of asthma in people who are aspirin-sensitive
- life-threatening skin reactions
- liver problems including liver failure
- new or worse high blood pressure
- heart failure
- kidney problems including kidney failure
- low red blood cells (anemia)

Other side effects of NSAIDs include:stomach pain, constipation, diarrhea, gas, heartburn, nausea, vomiting, and dizziness.

Get emergency help right away if you get any of the following symptoms:

- shortness of breath or trouble breathing
- chest pain
- weakness in one part or side of your body
- slurred speech
- swelling of the face or throat

Stop using diclofenac sodium gel and call your healthcare provider right away if you get any of the following symptoms:

• nausea

• more tired or weaker than usual

• diarrhea

• itching

• your skin or eyes look yellow

• indigestion or stomach pain

• flu-like symptoms

• vomit blood

• there is blood in your bowel movement or it is black and sticky like tar

• unusual weight gain

• skin rash or blisters with fever

• swelling of the arms, legs, hands and feet

Application site skin reactions are common with diclofenac sodium gel including:skin redness, itching, rash, dry skin, scaling, and peeling.

If you take too much NSAID, call your healthcare provider or get medical help right away.

- Diclofenac sodium gel may cause fertility problems in females, which may affect your ability to have a child. Talk to your healthcare provider if this a concern for you.
- These are not all of the possible side effects of NSAIDs. For more information, ask your healthcare provider or pharmacist about NSAIDs.

Call your doctor for medical advice about side effects. You may report side effects to FDA at 1-800-FDA-1088.

Other information about NSAIDs

- Aspirin is an NSAID but it does not increase the chance of a heart attack. Aspirin can cause bleeding in the brain, stomach, and intestines. Aspirin can also cause ulcers in the stomach and intestines.
- Some NSAIDs are sold in lower doses without a prescription (over-the-counter). Talk to your healthcare provider before using over-the-counter NSAIDs.

How should I store diclofenac sodium gel?

- Store diclofenac sodium gel at room temperature 68°F to 77°F (20°C to 25°C).
- Keep diclofenac sodium gel away from heat. Avoid freezing diclofenac sodium gel.

Keep diclofenac sodium gel and all medicines out of the reach of children.

General information about the safe and effective use of diclofenac sodium gel.

- Medicines are sometimes prescribed for purposes other than those listed in a Medication Guide. Do not use diclofenac sodium gel for a condition for which it was not prescribed. Do not give diclofenac sodium gel to other people, even if they have the same symptoms that you have. It may harm them. If you would like more information about diclofenac sodium gel, talk with your healthcare provider. You can ask your pharmacist or healthcare provider for information about diclofenac sodium gel that is written for health professionals.

What are the ingredients in diclofenac sodium gel?

Active ingredient:diclofenac sodium

Inactive ingredients:benzyl alcohol, sodium hyaluronate, polyethylene glycol monomethyl ether, and purified water.

Trademarks are the property of their respective owners.

Medication Guide available at

www.glenmarkpharma-us.com/medguides

Manufactured by:

Glenmark Pharmaceuticals Limited

Colvale-Bardez, Goa 403513, India

Manufactured for:

Glenmark Pharmaceuticals Inc., USA

Mahwah, NJ 07430

Questions? 1 (888) 721-7115

www.glenmarkpharma-us.com

1. This Medication Guide has been approved by the U.S. Food and Drug Administration Revised: 07/2023